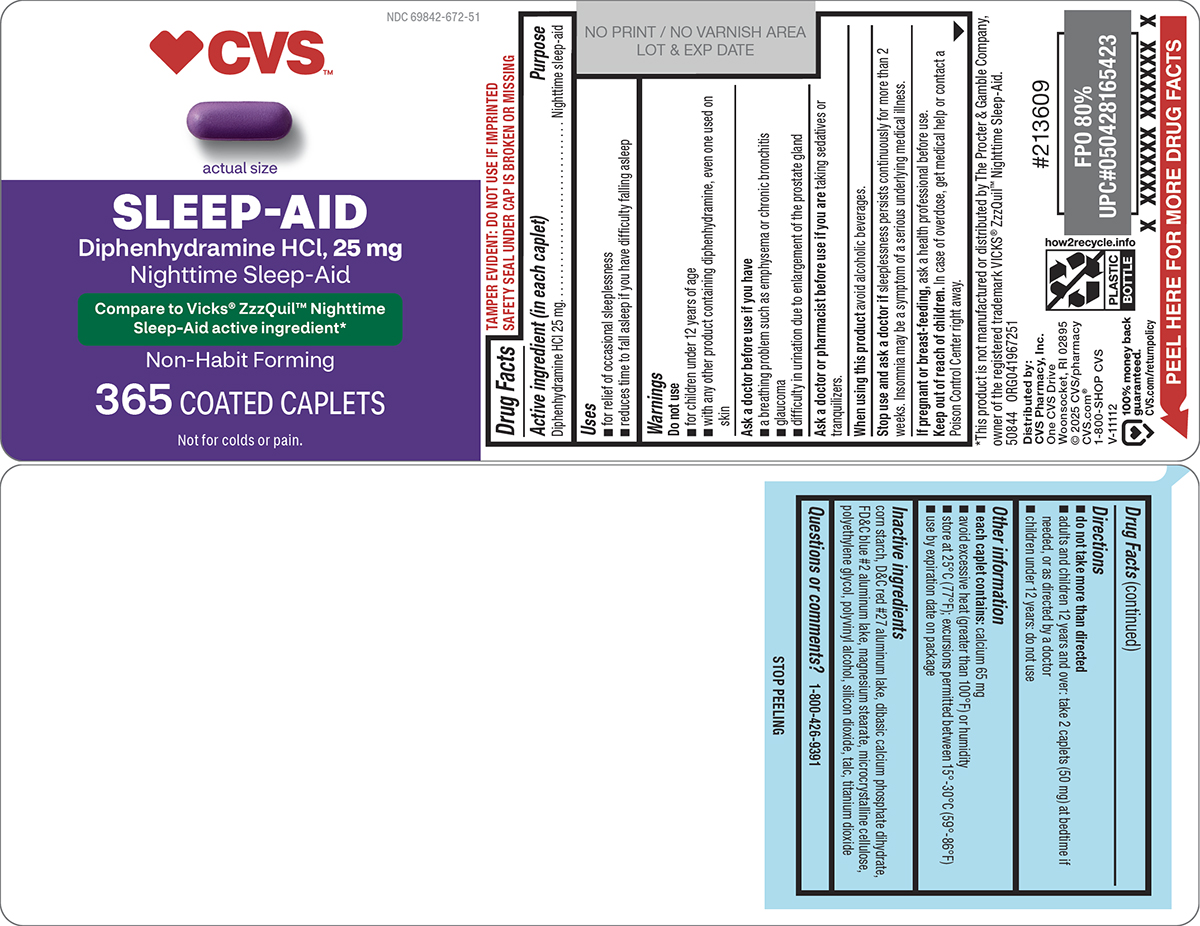 DRUG LABEL: Sleep-Aid
NDC: 69842-672 | Form: TABLET, FILM COATED
Manufacturer: CVS PHARMACY
Category: otc | Type: HUMAN OTC DRUG LABEL
Date: 20251117

ACTIVE INGREDIENTS: DIPHENHYDRAMINE HYDROCHLORIDE 25 mg/1 1
INACTIVE INGREDIENTS: STARCH, CORN; D&C RED NO. 27 ALUMINUM LAKE; DIBASIC CALCIUM PHOSPHATE DIHYDRATE; FD&C BLUE NO. 2 ALUMINUM LAKE; MAGNESIUM STEARATE; MICROCRYSTALLINE CELLULOSE; POLYETHYLENE GLYCOL, UNSPECIFIED; POLYVINYL ALCOHOL, UNSPECIFIED; SILICON DIOXIDE; TALC; TITANIUM DIOXIDE

CVS 44-672

Active ingredient (in each caplet)

Diphenhydramine HCl 25 mg

Purpose

Nighttime sleep-aid

Uses

- for relief of occasional sleeplessness
- reduces time to fall asleep if you have difficulty falling asleep

Warnings

Do not use

- for children under 12 years of age
- with any other product containing diphenhydramine, even one used on skin

Ask a doctor before use if you have

- a breathing problem such as emphysema or chronic bronchitis
- glaucoma
- difficulty in urination due to enlargement of the prostate gland

Ask a doctor or pharmacist before use if you are

taking sedatives or tranquilizers.

When using this product

avoid alcoholic beverages.

Stop use and ask a doctor if

sleeplessness persists continuously for more than 2 weeks. Insomnia may be a symptom of a serious underlying medical illness.

If pregnant or breast-feeding,

ask a health professional before use.

Keep out of reach of children.

In case of overdose, get medical help or contact a Poison Control Center right away.

Directions

- do not take more than directed
- adults and children 12 years and over: take 2 caplets (50 mg) at bedtime if needed, or as directed by a doctor
- children under 12 years: do not use

Other information

- each caplet contains: calcium 65 mg
- avoid excessive heat (greater than 100°F) or humidity
- store at 25°C (77°F); excursions permitted between 15°-30°C (59°-86°F)
- use by expiration date on package

Inactive ingredients

corn starch, D&C red #27 aluminum lake, dibasic calcium phosphate dihydrate, FD&C blue #2 aluminum lake, magnesium stearate, microcrystalline cellulose, polyethylene glycol, polyvinyl alcohol, silicon dioxide, talc, titanium dioxide

Questions or comments?

1-800-426-9391

Principal display panel

♥CVS™

NDC 69842-672-51

actual size

SLEEP-AID
Diphenhydramine HCl, 25 mg
Nighttime Sleep-Aid

Compare to Vicks® ZzzQuil™ Nighttime
Sleep-Aid active ingredient*

Non-Habit Forming

365 COATED CAPLETS

TAMPER EVIDENT: DO NOT USE IF IMPRINTED
SAFETY SEAL UNDER CAP IS BROKEN OR MISSING

*This product is not manufactured or distributed by The Procter & Gamble Company,
owner of the registered trademark VICKS® ZzzQuil™ Nighttime Sleep-Aid.
50844 ORG041967251

Distributed by:
CVS Pharmacy, Inc.
One CVS Drive
Woonsocket, RI 02895
© 2025 CVS/pharmacy
CVS.com®
1-800-SHOP CVS
V-11112

100% money back
guaranteed.
CVS.com/returnpolicy

CVS 44-672